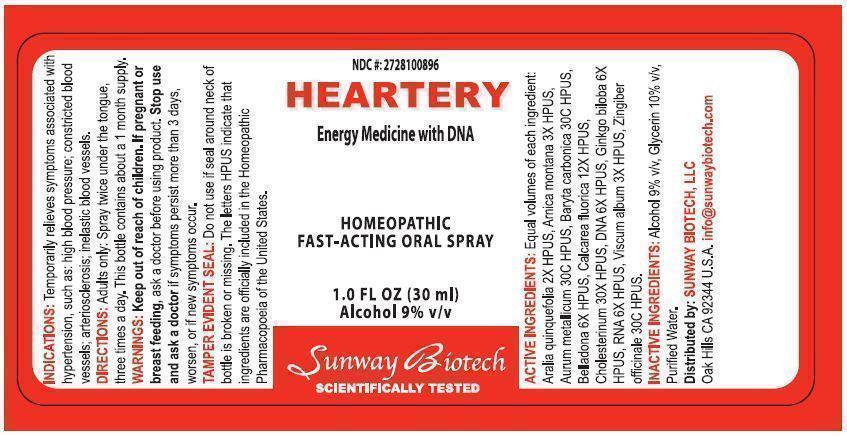 DRUG LABEL: Heartery
NDC: 27281-008 | Form: SPRAY
Manufacturer: Sunway Biotech LLC
Category: homeopathic | Type: HUMAN OTC DRUG LABEL
Date: 20131209

ACTIVE INGREDIENTS: AMERICAN GINSENG 1 [hp_C]/30 mL; ARNICA MONTANA 1.5 [hp_C]/30 mL; GOLD 30 [hp_C]/30 mL; BARIUM CARBONATE 30 [hp_C]/30 mL; ATROPA BELLADONNA 3 [hp_C]/30 mL; CALCIUM FLUORIDE 6 [hp_C]/30 mL; CHOLESTEROL 15 [hp_C]/30 mL; HERRING SPERM DNA 3 [hp_C]/30 mL; GINKGO 3 [hp_C]/30 mL; SACCHAROMYCES CEREVISIAE RNA 3 [hp_C]/30 mL; VISCUM ALBUM FRUITING TOP 1.5 [hp_C]/30 mL; GINGER 30 [hp_C]/30 mL
INACTIVE INGREDIENTS: ALCOHOL; GLYCERIN; WATER

ACTIVE INGREDIENT

Active Ingredients: Aralia Quinquefolia 2X HPUS, Arnica Montana 3X HPUS, Aurum Metallicum 30C HPUS,Baryta Carbonica 30C HPUS, Belladonna 6X HPUS, Calcarea Fluorica 12x HPUS, Cholesterinum 30X HPUS, DNA 6X HPUS, Ginkgo Biloba 6X HPUS, RNA 6X HPUS, Viscum Album 3X HPUS, Zingiber Officinale 30C HPUS.

PURPOSE

NDC #: 2728100896

HEARTERY

Energy Medicine with DNA

Homeopathic Fast-Acting Oral Spray

1.0 Fl. Oz. (30 mL)

Alcohol 9% v/v

Keep out of reach of children.

INDICATIONS AND USAGE

Indications: Temporarily relieves symptoms associated with hypertension, such as: high blood pressure; constricted blood vessels; arteriosclerosis; inelastic blood vessels.

DOSAGE AND ADMINISTRATION

Directions: Adults only: spray twice under the tongue, three times a day. This bottle contains about a 1 month supply.

WARNINGS

Warnings: Keep out of reach of children. If pregnant or breast feeding, ask a doctor before using product. Stop use and ask a doctor if symptoms persist more than 3 days, worsen, or new symptoms occur.

OTHER SAFETY INFORMATION

Tamper Evident Seal: Do not use if seal around neck of bottle is broken or missing. The letters HPUS indicate that ingredients are officially included in the Homeopathic Pharmacopoeia of the United States.

Distributed by:

SUNWAY BIOTECH, LLC

Oak Hills, CA 92344 U.S.A. info@sunwaybiotech.com

INACTIVE INGREDIENT

Inactive Ingredients: Alcohol 9% v/v, Glycerin 10% v/v, Purified Water.